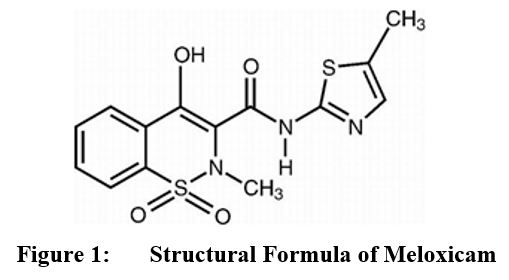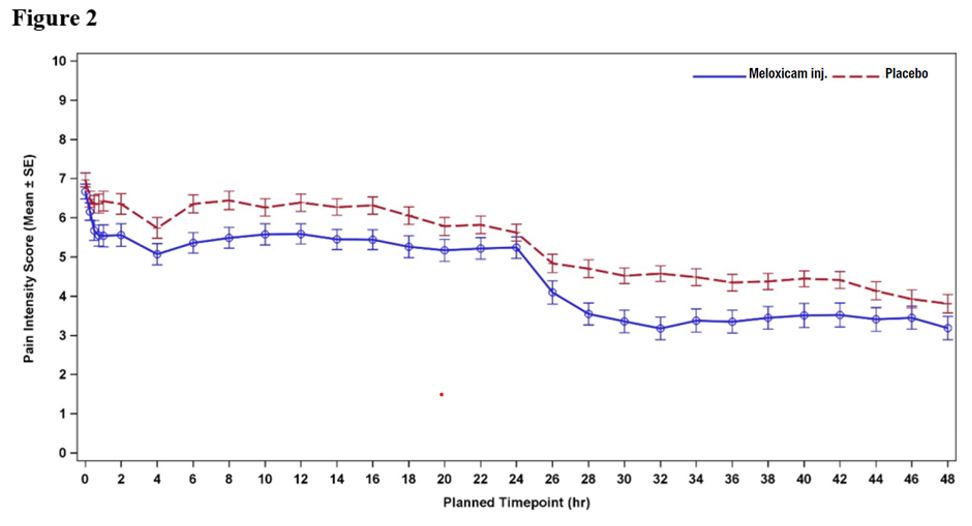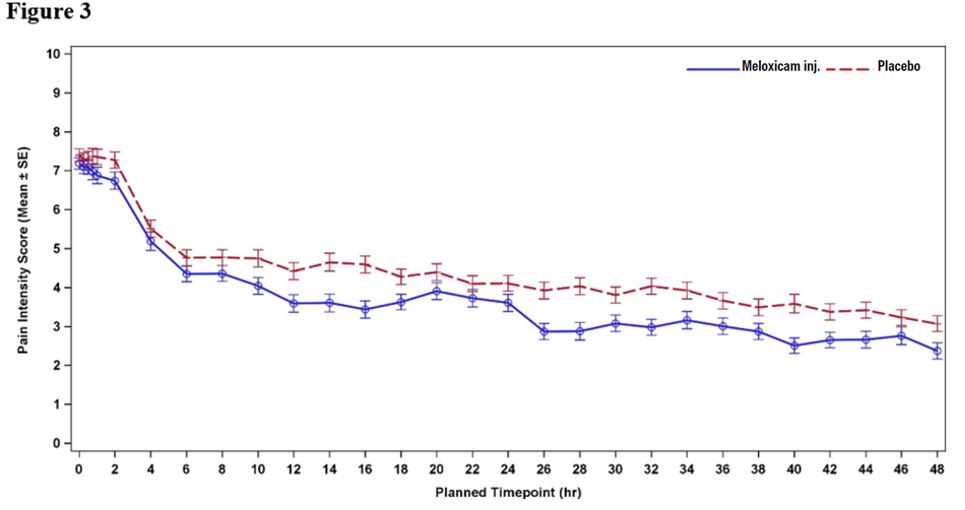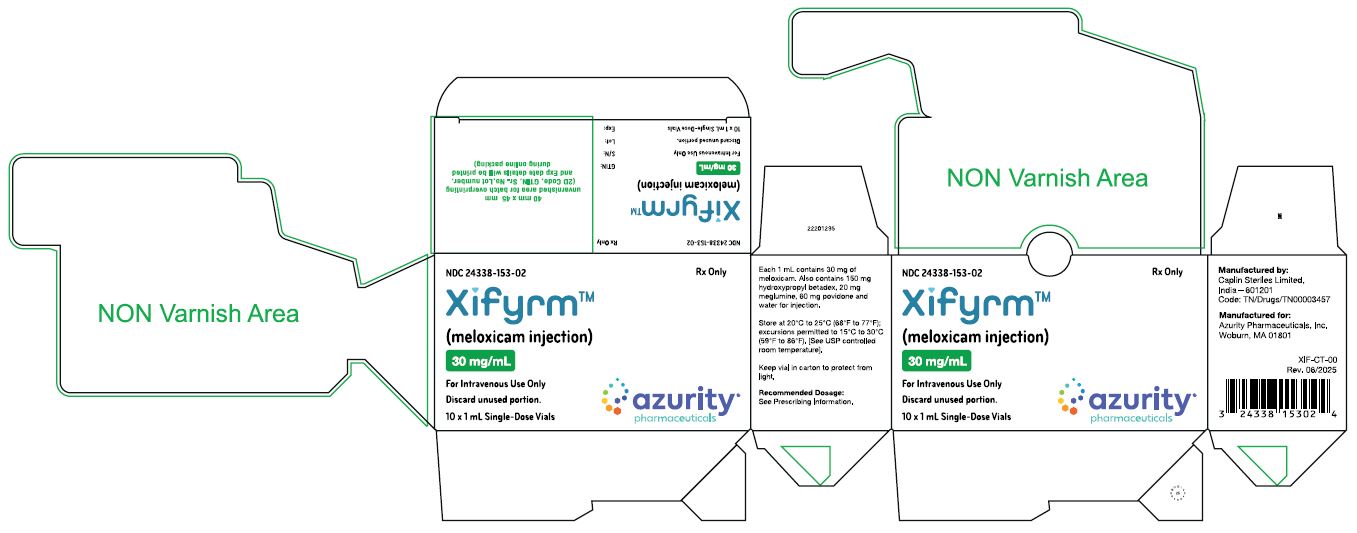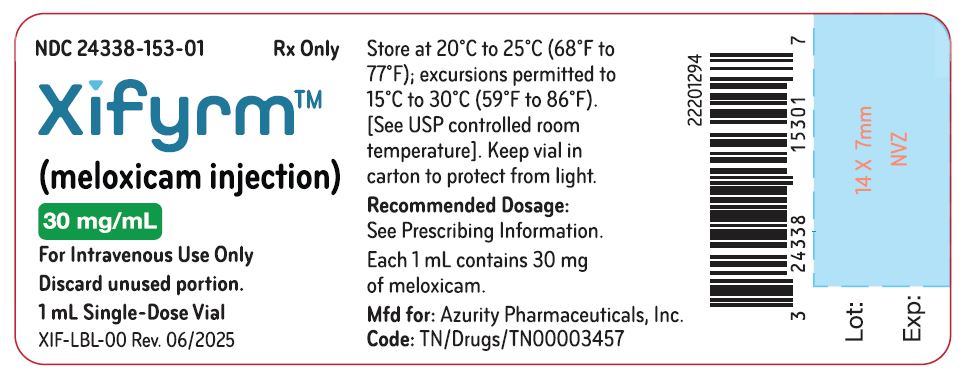 DRUG LABEL: XIFYRM
NDC: 24338-153 | Form: INJECTION
Manufacturer: Azurity Pharmaceuticals, Inc.
Category: prescription | Type: Human Prescription Drug Label
Date: 20250618

ACTIVE INGREDIENTS: MELOXICAM 30 mg/1 mL
INACTIVE INGREDIENTS: HYDROXYPROPYL BETADEX; MEGLUMINE; POVIDONE K12

HIGHLIGHTS OF PRESCRIBING INFORMATION

These highlights do not include all the information needed to use XIFYRM™ safely and effectively. See full prescribing information for XIFYRM™.
XIFYRM™ (meloxicam injection), for intravenous use
Initial U.S. Approval: 2000

WARNING: RISK OF SERIOUS CARDIOVASCULAR AND GASTROINTESTINAL EVENTS

See full prescribing information for complete boxed warning.
• Non-steroidal anti-inflammatory drugs (NSAIDs) cause an increased risk of serious cardiovascular thrombotic events, including myocardial infarction, and stroke, which can be fatal. This risk may occur early in treatment and may increase with duration of use (5.1)
• XIFYRM is contraindicated in the setting of coronary artery bypass graft (CABG) surgery (4, 5.1)
• NSAIDs cause an increased risk of serious gastrointestinal (GI) adverse events including bleeding, ulceration, and perforation of the stomach or intestines, which can be fatal. These events can occur at any time during use and without warning symptoms. Elderly patients and patients with a prior history of peptic ulcer disease and/or GI bleeding are at greater risk for serious GI events (5.2)

1 INDICATIONS AND USAGE

XIFYRM contains meloxicam, which is an NSAID, and is indicated for use in adults for the management of moderate-to-severe pain, alone or in combination with non-NSAID analgesics.
Limitation of Use
Because of delayed onset of analgesia, XIFYRM alone is not recommended for use when rapid onset of analgesia is required. (1)

2 DOSAGE AND ADMINISTRATION

• Use for the shortest duration consistent with individual patient treatment goals. (2)
• Recommended dosage: 30 mg once daily, administered by intravenous bolus injection over 15 seconds. (2)
• Monitor patient analgesic response and administer a short-acting, non-NSAID, immediate-release analgesic if response is inadequate. (2)
• Patients must be well hydrated before XIFYRM administration. (2)

3 DOSAGE FORMS AND STRENGTHS

XIFYRM (meloxicam injection), single-dose vial containing 30 mg/mL per vial. (3)

4 CONTRAINDICATIONS

• Known hypersensitivity to meloxicam or any components of the drug product. (4)
• History of asthma, urticaria, or other allergic-type reactions after taking aspirin or other NSAIDs. (4)
• In the setting of coronary artery bypass graft (CABG) surgery. (4)
• Moderate to severe renal insufficiency patients who are at risk for renal failure due to volume depletion. (4)

5 WARNINGS AND PRECAUTIONS

• Hepatotoxicity: Inform patients of warning signs and symptoms of hepatotoxicity. Discontinue XIFYRM immediately if abnormal liver tests persist or worsen or if clinical signs and symptoms of liver disease develop. (5.3)
• Hypertension: Patients taking some antihypertensive medications may have impaired response to these therapies when taking XIFYRM injection, monitor blood pressure. (5.4, 7)
• Heart Failure and Edema: Avoid use of XIFYRM in patients with severe heart failure unless benefits are expected to outweigh risk of worsening heart failure. (5.5)
• Renal Toxicity: Monitor renal function in patients with renal or hepatic impairment, heart failure, dehydration, or hypovolemia. Avoid use of XIFYRM in patients with advanced renal disease unless benefits are expected to outweigh risk of worsening renal function. (5.6)
• Anaphylactic Reactions: Seek emergency help if an anaphylactic reaction occurs. (5.7)
• Exacerbation of Asthma Related to Aspirin Sensitivity: XIFYRM is contraindicated in patients with aspirin-sensitive asthma. Monitor patients with preexisting asthma (without aspirin sensitivity). (5.8)
• Serious Skin Reactions: Discontinue XIFYRM at first appearance of skin rash or other signs of hypersensitivity. (5.9)
• Drug Reaction with Eosinophilia and Systemic Symptoms (DRESS): Discontinue and evaluate clinically. (5.10)
• Hematologic Toxicity: Monitor hemoglobin or hematocrit in patients with any signs or symptoms of anemia. (5.12, 7)
• Fetal Toxicity: Limit use of NSAIDs, including XIFYRM, between about 20 to 30 weeks in pregnancy due to the risk of renal oligohydramnios/fetal dysfunction. Avoid use of NSAIDs in women at about 30 weeks gestation and later in pregnancy due to the risks of oligohydramnios/fetal renal dysfunction and premature closure of the fetal ductus arteriosus. (5.11, 8.1)

6 ADVERSE REACTIONS

The most common adverse reactions (≥ 2% and greater than placebo) in controlled clinical trials include constipation, GGT increased, and anemia. (6)

To report SUSPECTED ADVERSE REACTIONS, contact Azurity Pharmaceuticals, Inc. at 1-800-461-7449 or FDA at 1-800-FDA-1088 or www.fda.gov/medwatch.

7 DRUG INTERACTIONS

• Drugs that Interfere with Hemostasis (e.g., warfarin, aspirin, SSRIs/SNRIs): Monitor patients for bleeding who are concomitantly taking XIFYRM with drugs that interfere with hemostasis. Concomitant use of XIFYRM and analgesic doses of aspirin is not generally recommended. (7)
• ACE Inhibitors, Angiotensin Receptor Blockers (ARBs), or Beta-Blockers: Concomitant use with XIFYRM may diminish the antihypertensive effect of these drugs. Monitor blood pressure. (7)
• ACE Inhibitors and ARBs: Concomitant use with XIFYRM in elderly, volume-depleted, or those with renal impairment may result in deterioration of renal function. In such high risk patients, monitor for signs of worsening renal function. (7)
• Diuretics: NSAIDs can reduce natriuretic effect of furosemide and thiazide diuretics. Monitor patients to assure diuretic efficacy including antihypertensive effects. (7)

8 USE IN SPECIFIC POPULATIONS

• Infertility: NSAIDs are associated with reversible infertility. Consider withdrawal of XIFYRM in women who have difficulties conceiving. (8.3)

FULL PRESCRIBING INFORMATION

WARNING: RISK OF SERIOUS CARDIOVASCULAR AND GASTROINTESTINAL EVENTS

Cardiovascular Risk
• Non-steroidal anti-inflammatory drugs (NSAIDs) cause an increased risk of serious cardiovascular thrombotic events including myocardial infarction and stroke, which can be fatal. This risk may occur early in treatment and may increase with duration of use. [see Warnings and Precautions (5.1)].
• XIFYRM is contraindicated in the setting of coronary artery bypass graft (CABG) surgery [see Contraindications (4) and Warnings and Precautions (5.1)].

Gastrointestinal Risk
• NSAIDs cause an increased risk of serious gastrointestinal (GI) adverse events including bleeding, ulceration, and perforation of the stomach or intestines, which can be fatal. These events can occur at any time during use and without warning symptoms. Elderly patients and patients with a prior history of peptic ulcer disease and/or GI bleeding are at greater risk for serious GI events [see Warnings and Precautions (5.2)].

1 INDICATIONS AND USAGE

XIFYRM is indicated for use in adults for the management of moderate-to-severe pain, alone or in combination with non-NSAID analgesics.
Limitation of Use
Because of delayed onset of analgesia, XIFYRM alone is not recommended for use when rapid onset of analgesia is required.

2 DOSAGE AND ADMINISTRATION

Use for the shortest duration consistent with individual patient treatment goals [see Warnings and Precautions (5)].
For intravenous administration only.
The recommended dosage of XIFYRM is 30 mg once daily, administered by intravenous bolus injection over 15 seconds.
When initiating XIFYRM, monitor patient analgesic response. Because the median time to meaningful pain relief was 2 and 3 hours after XIFYRM administration in two clinical studies, a non-NSAID analgesic with a rapid onset of effect may be needed, for example, upon anesthetic emergence or resolution of local or regional anesthetic blocks [see Clinical Studies (14)].
Some patients may not experience adequate analgesia for the entire 24-hour dosing interval and may require administration of a short-acting, non-NSAID, immediate-release analgesic [see Clinical Studies (14)].
To reduce the risk of renal toxicity, patients must be well hydrated prior to administration of XIFYRM.
Visually inspect parenteral drug products for particulate matter and discoloration prior to administration. Should the contents appear discolored or contain particulate matter, discard the vial [see Dosage Forms and Strengths (3)].

3 DOSAGE FORMS AND STRENGTHS

XIFYRM (meloxicam injection) is a sterile, clear, pale yellow to yellow color solution intended for intravenous use available as a clear, single-dose vial containing 30 mg/mL per vial.

4 CONTRAINDICATIONS

XIFYRM is contraindicated in the following patients:
• Known hypersensitivity (e.g., anaphylactic reactions and serious skin reactions) to meloxicam or any components of the drug product [see Warnings and Precautions (5.7)].
• History of asthma, urticaria, or other allergic-type reactions after taking aspirin or other NSAIDs. Severe, sometimes fatal anaphylactic-like reactions to NSAIDs have been reported in such patients [see Warnings and Precautions (5.8)].
• In the setting of coronary artery bypass graft (CABG) surgery [see Warnings and Precautions (5.1)].
• Moderate to severe renal insufficiency patients who are at risk for renal failure due to volume depletion [see Warnings and Precautions (5.6)].

5 WARNINGS AND PRECAUTIONS

5.1 Cardiovascular Thrombotic Events

Clinical trials of several COX-2 selective and nonselective NSAIDs of up to three years duration have shown an increased risk of serious cardiovascular (CV) thrombotic events, including myocardial infarction (MI) and stroke, which can be fatal. Based on available data, it is unclear that the risk for CV thrombotic events is similar for all NSAIDs. The relative increase in serious CV thrombotic events over baseline conferred by NSAID use appears to be similar in those with and without known CV disease or risk factors for CV disease. However, patients with known CV disease or risk factors had a higher absolute incidence of excess serious CV thrombotic events, due to their increased baseline rate. Some observational studies found that this increased risk of serious CV thrombotic events began as early as the first weeks of treatment. The increase in CV thrombotic risk has been observed most consistently at higher doses.
To minimize the potential risk for an adverse CV event in NSAID-treated patients, use the lowest effective dose for the shortest duration possible. Physicians and patients should remain alert for the development of such events, throughout the entire treatment course, even in the absence of previous CV symptoms. Patients should be informed about the symptoms of serious CV events and the steps to take if they occur.
There is no consistent evidence that concurrent use of aspirin mitigates the increased risk of serious CV thrombotic events associated with NSAID use. The concurrent use of aspirin and an NSAID, such as meloxicam, increases the risk of serious gastrointestinal (GI) events [see Warnings and Precautions (5.2)].

Status Post Coronary Artery Bypass Graft (CABG) Surgery
Two large, controlled clinical trials of a COX-2 selective NSAID for the treatment of pain in the first 10-14 days following CABG surgery found an increased incidence of myocardial infarction and stroke. NSAIDs are contraindicated in the setting of CABG [see Contraindications (4)].

Post-MI Patients
Observational studies conducted in the Danish National Registry have demonstrated that patients treated with NSAIDs in the post-MI period were at increased risk of reinfarction, CV-related death, and all-cause mortality beginning in the first week of treatment. In this same cohort, the incidence of death in the first year post-MI was 20 per 100 person years in NSAID-treated patients compared to 12 per 100 person years in non-NSAID exposed patients. Although the absolute rate of death declined somewhat after the first year post-MI, the increased relative risk of death in NSAID users persisted over at least the next four years of follow-up.

Avoid the use of XIFYRM in patients with a recent MI unless the benefits are expected to outweigh the risk of recurrent CV thrombotic events. If XIFYRM is used in patients with a recent MI, monitor patients for signs of cardiac ischemia.

5.2 Gastrointestinal Effects- Risk of Ulceration, Bleeding, and Perforation

NSAIDs, including meloxicam, can cause serious gastrointestinal (GI) adverse events including inflammation, bleeding, ulceration, and perforation of the esophagus, stomach, small intestine, or large intestine, which can be fatal. These serious adverse events can occur at any time, with or without warning symptoms, in patients treated with XIFYRM. Only one in five patients who develop a serious upper GI adverse event on NSAID therapy is symptomatic. Upper GI ulcers, gross bleeding, or perforation caused by NSAIDs occurred in approximately 1% of patients treated for 3-6 months, and in about 2-4% of patients treated for one year. However, even short- term NSAID therapy is not without risk.

Risk Factors for GI Bleeding, Ulceration, and Perforation
Patients with a prior history of peptic ulcer disease and/or GI bleeding who used NSAIDs had a greater than 10-fold increased risk for developing a GI bleed compared to patients without these risk factors. Other factors that increase the risk of GI bleeding in patients treated with NSAIDs include longer duration of NSAID therapy; concomitant use of oral corticosteroids, aspirin, anticoagulants, or selective serotonin reuptake inhibitors (SSRIs); smoking; use of alcohol; older age; and poor general health status. Most postmarketing reports of fatal GI events occurred in elderly or debilitated patients. Additionally, patients with advanced liver disease and/or coagulopathy are at increased risk for GI bleeding.
Strategies to Minimize the GI Risks in NSAID-treated patients:
• Use the lowest effective dosage for the shortest possible duration.
• Avoid administration of more than one NSAID at a time.
• Avoid use in patients at higher risk unless benefits are expected to outweigh the increased risk of bleeding. For such patients, as well as those with active GI bleeding, consider alternate therapies other than NSAIDs.
• Remain alert for signs and symptoms of GI ulceration and bleeding during NSAID therapy.
• If a serious GI adverse event is suspected, promptly initiate evaluation and treatment, and discontinue XIFYRM until a serious GI adverse event is ruled out.
• In the setting of concomitant use of low-dose aspirin for cardiac prophylaxis, monitor patients more closely for evidence of GI bleeding [see Drug Interactions (7)].

5.3 Hepatotoxicity

Elevations of ALT or AST (three or more times the upper limit of normal [ULN]) have been reported in approximately 1% of NSAID-treated patients in clinical trials. In addition, rare, sometimes fatal, cases of severe hepatic injury, including fulminant hepatitis, liver necrosis, and hepatic failure have been reported.
Elevations of ALT or AST (less than three times ULN) may occur in up to 15% of patients treated with NSAIDs including meloxicam.
Inform patients of the warning signs and symptoms of hepatotoxicity (e.g., nausea, fatigue, lethargy, diarrhea, pruritus, jaundice, right upper quadrant tenderness, and "flu-like" symptoms). If clinical signs and symptoms consistent with liver disease develop, or if systemic manifestations occur (e.g., eosinophilia, rash, etc.), discontinue XIFYRM immediately, and perform a clinical evaluation of the patient [see Use in Specific Populations (8.6) and Clinical Pharmacology (12.3)].

5.4 Hypertension

NSAIDs, including XIFYRM, can lead to new onset of hypertension or worsening of pre-existing hypertension, either of which may contribute to the increased incidence of CV events. Patients taking angiotensin converting enzyme (ACE) inhibitors, thiazides or loop diuretics may have impaired response to these therapies when taking NSAIDs [see Drug Interactions (7)].
Monitor blood pressure (BP) during the initiation of NSAID treatment and throughout the course of therapy.

5.5 Heart Failure and Edema

The Coxib and traditional NSAID Trialists’ Collaboration meta-analysis of randomized controlled trials demonstrated an approximately two-fold increase in hospitalizations for heart failure in COX-2 selective-treated patients and nonselective NSAID-treated patients compared to placebo-treated patients. In a Danish National Registry study of patients with heart failure, NSAID use increased the risk of MI, hospitalization for heart failure, and death.
Additionally, fluid retention and edema have been observed in some patients treated with NSAIDs. Use of meloxicam may blunt the CV effects of several therapeutic agents used to treat these medical conditions (e.g., diuretics, ACE inhibitors, or angiotensin receptor blockers [ARBs]) [see Drug Interactions (7)].
Avoid the use of XIFYRM in patients with severe heart failure unless the benefits are expected to outweigh the risk of worsening heart failure. If XIFYRM is used in patients with severe heart failure, monitor patients for signs of worsening heart failure.

5.6 Renal Toxicity and Hyperkalemia

Renal Toxicity
Long-term administration of NSAIDs has resulted in renal papillary necrosis, renal insufficiency, acute renal failure, and other renal injury.
Renal toxicity has also been seen in patients in whom renal prostaglandins have a compensatory role in the maintenance of renal perfusion. In these patients, administration of an NSAID may cause a dose-dependent reduction in prostaglandin formation and, secondarily, in renal blood flow, which may precipitate overt renal decompensation. Patients at greatest risk of this reaction are those with impaired renal function, dehydration, hypovolemia, heart failure, liver dysfunction, those taking diuretics and ACE inhibitors or ARBs, and the elderly. Discontinuation of NSAID therapy is usually followed by recovery to the pretreatment state.
XIFYRM is not recommended in patients with moderate to severe renal insufficiency and is contraindicated in patients with moderate to severe renal insufficiency who are at risk for renal failure due to volume depletion.
No information is available from controlled clinical studies regarding the use of XIFYRM in patients with advanced renal disease. The renal effects of XIFYRM may hasten the progression of renal dysfunction in patients with pre-existing renal disease.
Correct volume status in dehydrated or hypovolemic patients prior to initiating XIFYRM. Monitor renal function in patients with renal or hepatic impairment, heart failure, dehydration, or hypovolemia during use of XIFYRM [see Drug Interactions (7)]. Avoid the use of XIFYRM in patients with advanced renal disease unless the benefits are expected to outweigh the risk of worsening renal function. If XIFYRM is used in patients with advanced renal disease, monitor patients for signs of worsening renal function [see Clinical Pharmacology (12.3)].

Hyperkalemia
Increases in serum potassium concentration, including hyperkalemia, have been reported with use of NSAIDs, even in some patients without renal impairment. In patients with normal renal function, these effects have been attributed to a hyporeninemic-hypoaldosteronism state.

5.7 Anaphylactic Reactions

Meloxicam has been associated with anaphylactic reactions in patients with and without known hypersensitivity to meloxicam and in patients with aspirin-sensitive asthma [see Contraindications (4) and Warnings and Precautions (5.8)].
Seek emergency help if an anaphylactic reaction occurs.

5.8 Exacerbation of Asthma Related to Aspirin Sensitivity

A subpopulation of patients with asthma may have aspirin-sensitive asthma which may include chronic rhinosinusitis complicated by nasal polyps; severe, potentially fatal bronchospasm; and/or intolerance to aspirin and other NSAIDs. Because cross-reactivity between aspirin and other NSAIDs has been reported in such aspirin-sensitive patients, XIFYRM is contraindicated in patients with this form of aspirin sensitivity [see Contraindications (4)]. When XIFYRM is used in patients with preexisting asthma (without known aspirin sensitivity), monitor patients for changes in the signs and symptoms of asthma.

5.9 Serious Skin Reactions

NSAIDs, including XIFYRM, can cause serious skin adverse events such as exfoliative dermatitis, Stevens-Johnson Syndrome (SJS), and toxic epidermal necrolysis (TEN), which can be fatal. These serious events may occur without warning. Patients should be informed about the signs and symptoms of serious skin manifestations and use of the drug should be discontinued at the first appearance of skin rash or any other sign of hypersensitivity. XIFYRM is contraindicated in patients with previous serious skin reactions to NSAIDs [see Contraindications (4)].

5.10 Drug Reaction with Eosinophilia and Systemic Symptoms (DRESS)

Drug Reaction with Eosinophilia and Systemic Symptoms (DRESS) has been reported in patients taking NSAIDs such as XIFYRM. Some of these events have been fatal or life- threatening. DRESS typically, although not exclusively, presents with fever, rash, lymphadenopathy, and/or facial swelling. Other clinical manifestations may include hepatitis, nephritis, hematological abnormalities, myocarditis, or myositis. Sometimes symptoms of DRESS may resemble an acute viral infection. Eosinophilia is often present. Because this disorder is variable in its presentation, other organ systems not noted here may be involved. It is important to note that early manifestations of hypersensitivity, such as fever or lymphadenopathy, may be present even though rash is not evident. If such signs or symptoms are present, discontinue XIFYRM and evaluate the patient immediately.

5.11 Fetal Toxicity

Premature Closure of Fetal Ductus Arteriosus
Avoid use of NSAIDs, including XIFYRM, in pregnant women at about 30 weeks gestation and later. NSAIDs, including XIFYRM, increase the risk of premature closure of the fetal ductus arteriosus at approximately this gestational age.

Oligohydramnios/Neonatal Renal Impairment
Use of NSAIDs, including XIFYRM, at about 20 weeks gestation or later in pregnancy may cause fetal renal dysfunction leading to oligohydramnios and, in some cases, neonatal renal impairment. These adverse outcomes are seen, on average, after days to weeks of treatment, although oligohydramnios has been infrequently reported as soon as 48 hours after NSAID initiation. Oligohydramnios is often, but not always, reversible with treatment discontinuation. Complications of prolonged oligohydramnios may, for example, include limb contractures and delayed lung maturation. In some postmarketing cases of impaired neonatal renal function, invasive procedures such as exchange transfusion or dialysis were required.

If NSAID treatment is necessary between about 20 weeks and 30 weeks gestation, limit XIFYRM use to the lowest effective dose and shortest duration possible. Consider ultrasound monitoring of amniotic fluid if XIFYRM treatment extends beyond 48 hours. Discontinue XIFYRM if oligohydramnios occurs and follow up according to clinical practice [see Use in Specific Populations (8.1)]

5.12 Hematologic Toxicity

Anemia has occurred in NSAID-treated patients. This may be due to occult or gross blood loss, fluid retention, or an incompletely described effect on erythropoiesis. If a patient treated with XIFYRM has any signs or symptoms of anemia, monitor hemoglobin or hematocrit.
NSAIDs, including XIFYRM, may increase the risk of bleeding events. Co-morbid conditions such as coagulation disorders or concomitant use of warfarin, other anticoagulants, antiplatelet agents (e.g., aspirin), serotonin reuptake inhibitors (SSRIs) and serotonin norepinephrine reuptake inhibitors (SNRIs) may increase this risk. Monitor these patients for signs of bleeding [see Drug Interactions (7)].

5.13 Masking of Inflammation and Fever

The pharmacological activity of XIFYRM in reducing inflammation, and possibly fever, may diminish the utility of diagnostic signs in detecting infections.

5.14 Laboratory Monitoring

Because serious GI bleeding, hepatotoxicity, and renal injury can occur without warning symptoms or signs, consider monitoring patients on long-term NSAID treatment with a CBC and a chemistry profile periodically [see Warnings and Precautions (5.2, 5.3, 5.6)]. XIFYRM is not indicated for long-term treatment.

6 ADVERSE REACTIONS

The following adverse reactions are discussed in greater detail in the other sections of the labeling:
• Cardiovascular Thrombotic Events [see Warnings and Precautions (5.1)]
• GI Bleeding, Ulceration, and Perforation [see Warnings and Precautions (5.2)]
• Hepatotoxicity [see Warnings and Precautions (5.3)]
• Hypertension [see Warnings and Precautions (5.4)]
• Heart Failure and Edema [see Warnings and Precautions (5.5)]
• Renal Toxicity and Hyperkalemia [see Warnings and Precautions (5.6)]
• Anaphylactic Reactions [see Warnings and Precautions (5.7)]
• Serious Skin Reactions [see Warnings and Precautions (5.9)]
• Hematologic Toxicity [see Warnings and Precautions (5.12)]

6.1 Clinical Trials Experience

Because clinical trials are conducted under widely varying conditions, adverse reaction rates observed in the clinical trials of a drug cannot be directly compared to rates in the clinical trials of another drug and may not reflect the rates observed in practice.
During clinical development, 1426 patients were exposed to meloxicam injection in controlled and open- label Phase 2 and Phase 3 trials. Meloxicam injection was studied across a range of surgical procedures, including bunionectomy, abdominoplasty, soft tissue surgery, total knee replacement surgery, gynecologic surgery, complex foot surgery and total hip replacement surgery. In these trials, 381 patients received a single dose of meloxicam injection and 1045 patients received multiple doses of meloxicam injection daily for up to 7 days. The incidence rates of adverse reactions listed in Table 1 are derived from the three Phase 3 trials comparing meloxicam injection to placebo in patients who may have also received opioid rescue medication.

Table 1: Proportion of Patients Experiencing Common Adverse Reactions in Placebo- Controlled Phase 3 Clinical Trials occurring in greater than or equal to 2% of Patients Treated with Meloxicam injection and at a greater frequency than Placebo

Meloxicam injection |  | Placebo
Adverse Reaction | N=748 | N=393
Constipation | 57 (7.6%) | 24 (6.1%)
Gamma-Glutamyl transferase Increased | 21 (2.8%) | 6 (1.5%)
Anemia | 18 (2.4%) | 4 (1.0%)

The following is a list of adverse drug reactions occurring in <2% of patients receiving meloxicam injection in clinical trials.

Table 2: Additional Adverse Reactions for Meloxicam Injection

Body as a Whole | asthenia, back pain, edema, fatigue, hyperthermia, infusion site reactions (including pain, pruritus, phlebitis and thrombosis), muscle spasms, non-cardiac chest pain, pyrexia, vaginal discharge, weight decrease
Central and Peripheral Nervous System | disturbance in attention, migraine, presyncope, somnolence, syncope
Gastrointestinal | abdominal discomfort, abdominal distension, abdominal pain, diarrhea, dry mouth, epigastric discomfort, flatulence, frequent bowel movements, gastritis, gastroesophageal reflux, gastrointestinal pain, rectal hemorrhage
Heart Rate and Rhythm | tachycardia
Hematologic | increased bleeding time, neutropenia, thrombocytosis
Infections and Infestations | cellulitis, gastroenteritis, urinary tract infection, vulval abscess
Liver and Biliary System | liver function test abnormal
Metabolic and Nutritional | hypokalemia, hypomagnesemia
Procedural Complications | incision site hemorrhage, incision site rash, wound dehiscence, wound hematoma
Psychiatric | confusion, hallucination, insomnia
Respiratory | dyspnea, epistaxis, hypoxia, oropharyngeal pain
Skin and Appendages | contact dermatitis, ecchymosis, rash
Urinary System | pollakiuria, urinary retention

6.2 Postmarketing Experience

The following adverse reactions have been identified during post-approval use of meloxicam. Because these reactions are reported voluntarily from a population of uncertain size, it is not always possible to reliably estimate their frequency or establish a causal relationship to drug exposure.
Adverse reactions reported in worldwide post marketing experience or the literature include: acute urinary retention; agranulocytosis; alterations in mood (such as mood elevation); anaphylactoid reactions including shock; erythema multiforme; exfoliative dermatitis; interstitial nephritis; jaundice; liver failure; Stevens-Johnson syndrome; toxic epidermal necrolysis, and infertility female.

7 DRUG INTERACTIONS

See Table 3 for clinically significant drug interactions with meloxicam.

Table 3: Clinically Significant Drug Interactions with Meloxicam

Drugs That Interfere with Hemostasis
Clinical Impact: | - Meloxicam and anticoagulants such as warfarin have a synergistic effect on bleeding. The concomitant use of meloxicam and anticoagulants have an increased risk of serious bleeding compared to the use of either drug alone. - Serotonin release by platelets plays an important role in hemostasis. Case- control and cohort epidemiological studies showed that concomitant use of drugs that interfere with serotonin reuptake and an NSAID may potentiate the risk of bleeding more than an NSAID alone.
Intervention: | Monitor patients with concomitant use of XIFYRM with anticoagulants (e.g., warfarin), antiplatelet agents (e.g., aspirin), selective serotonin reuptake inhibitors (SSRIs), and serotonin norepinephrine reuptake inhibitors (SNRIs) for signs of bleeding [see Warnings and Precautions (5.12)].
Aspirin
Clinical Impact: | Controlled clinical studies showed that the concomitant use of NSAIDs and analgesic doses of aspirin does not produce any greater therapeutic effect than the use of NSAIDs alone. In a clinical study, the concomitant use of an NSAID and aspirin was associated with a significantly increased incidence of GI adverse reactions as compared to use of the NSAID alone [see Warnings and Precautions (5.2)].
Intervention: | Concomitant use of XIFYRM and analgesic doses of aspirin is not generally recommended because of the increased risk of bleeding [see Warnings and Precautions (5.12)]. In the setting of concomitant use of low-dose aspirin for cardiac prophylaxis, monitor patients more closely for evidence of GI bleeding [see Warnings and Precautions (5.2)]. XIFYRM is not a substitute for low dose aspirin for cardiovascular protection.
ACE Inhibitors, Angiotensin Receptor Blockers, and Beta-Blockers
Clinical Impact: | - NSAIDs may diminish the antihypertensive effect of angiotensin converting enzyme (ACE) inhibitors, angiotensin receptor blockers (ARBs), or beta- blockers (including propranolol). - In patients who are elderly, volume-depleted (including those on diuretic therapy), or have renal impairment, co-administration of an NSAID with ACE inhibitors or ARBs may result in deterioration of renal function, including possible acute renal failure. These effects are usually reversible.
Intervention: | - During concomitant use of XIFYRM and ACE-inhibitors, ARBs, or beta- blockers, monitor blood pressure to ensure that the desired blood pressure is obtained. - During concomitant use of XIFYRM and ACE-inhibitors or ARBs in patients who are elderly, volume-depleted, or have impaired renal function, monitor for signs of worsening renal function [see Warnings and Precautions (5.6)]. - When these drugs are administered concomitantly, patients should be adequately hydrated. Assess renal function at the beginning of the concomitant treatment and periodically thereafter.
Diuretics
Clinical Impact: | Clinical studies, as well as post-marketing observations, showed that NSAIDs reduced the natriuretic effect of loop diuretics (e.g., furosemide) and thiazide diuretics in some patients. This effect has been attributed to the NSAID inhibition of renal prostaglandin synthesis. However, studies with furosemide agents and meloxicam have not demonstrated a reduction in natriuretic effect. Furosemide single and multiple dose pharmacodynamics and pharmacokinetics are not affected by multiple doses of meloxicam.
Intervention: | During concomitant use of XIFYRM with diuretics, observe patients for signs of worsening renal function, in addition to assuring diuretic efficacy including antihypertensive effects [see Warnings and Precautions (5.6)].
Lithium
Clinical Impact: | NSAIDs have produced elevations in plasma lithium levels and reductions in renal lithium clearance. The mean minimum lithium concentration increased 15%, and the renal clearance decreased by approximately 20%. This effect has been attributed to NSAID inhibition of renal prostaglandin synthesis. [see Clinical Pharmacology (12.3)].
Intervention: | During concomitant use of XIFYRM and lithium, monitor patients for signs of lithium toxicity.
Methotrexate
Clinical Impact: | Concomitant use of NSAIDs and methotrexate may increase the risk for methotrexate toxicity (e.g., neutropenia, thrombocytopenia, renal dysfunction).
Intervention: | During concomitant use of XIFYRM and methotrexate, monitor patients for methotrexate toxicity.
Cyclosporine
Clinical Impact: | Concomitant use of XIFYRM and cyclosporine may increase cyclosporine’s nephrotoxicity.
Intervention: | During concomitant use of XIFYRM and cyclosporine, monitor patients for signs of worsening renal function.
NSAIDs and Salicylates
Clinical Impact: | Concomitant use of meloxicam with other NSAIDs or salicylates (e.g., diflunisal, salsalate) increases the risk of GI toxicity, with little or no increase in efficacy [see Warnings and Precautions (5.2)].
Intervention: | The concomitant use of meloxicam with other NSAIDs or salicylates is not recommended.
Pemetrexed
Clinical Impact: | Concomitant use of XIFYRM and pemetrexed may increase the risk of pemetrexed-associated myelosuppression, renal, and GI toxicity (see the pemetrexed prescribing information).
Intervention: | During concomitant use of XIFYRM and pemetrexed, in patients with renal impairment whose creatinine clearance ranges from 45 to 79 mL/min, monitor for myelosuppression, renal and GI toxicity. Patients taking meloxicam should interrupt dosing for at least five days before, the day of, and two days following pemetrexed administration. In patients with creatinine clearance below 45 mL/min, the concomitant administration of meloxicam with pemetrexed is not recommended.
CYP2C9 Inhibitors
Clinical Impact: | In vitro studies indicate that CYP2C9 (cytochrome P450 metabolizing enzyme) plays an important role in this metabolic pathway with a minor contribution of the CYP3A4 isozyme. Thus concomitant usage of CYP2C9 inhibitors (such as amiodarone, fluconazole, and sulphaphenazole) may lead to abnormally high plasma levels of meloxicam due to reduced metabolic clearance [see Use in Specific Populations (8.8); and Clinical Pharmacology (12.3, 12.5)].
Intervention: | Consider dose reduction in patients undergoing treatment with CYP2C9 inhibitors, and monitor patients for adverse effects.

8 USE IN SPECIFIC POPULATIONS

8.1 Pregnancy

Risk Summary
Use of NSAIDs, including XIFYRM, can cause premature closure of the fetal ductus arteriosus and fetal renal dysfunction leading to oligohydramnios and, in some cases, neonatal renal impairment. Because of these risks, limit dose and duration of XIFYRM use between about 20 and 30 weeks of gestation, and avoid XIFYRM use at about 30 weeks of gestation and later in pregnancy (see Clinical Considerations, Data).

Premature Closure of Fetal Ductus Arteriosus
Use of NSAIDs, including XIFYRM, at about 30 weeks gestation or later in pregnancy increases the risk of premature closure of the fetal ductus arteriosus.

Oligohydramnios/Neonatal Renal Impairment
Use of NSAIDs at about 20 weeks gestation or later in pregnancy has been associated with cases of fetal renal dysfunction leading to oligohydramnios, and in some cases, neonatal renal impairment.
Data from observational studies regarding potential embryofetal risks of NSAID use in women in the first or second trimesters of pregnancy are inconclusive.
In animal reproduction studies, embryofetal death was observed in rats and rabbits treated during the period of organogenesis with meloxicam at oral doses equivalent to 0.32- and 3.24-times the maximum recommended human dose (MRHD) of 30 mg of XIFYRM. Increased incidence of septal heart defects were observed in rabbits treated throughout embryogenesis with meloxicam at an oral dose equivalent to 39-times the MRHD. In pre- and post-natal reproduction studies, there was an increased incidence of dystocia, delayed parturition, and decreased offspring survival at 0.04-times the MRHD. No teratogenic effects were observed in rats and rabbits treated with meloxicam during organogenesis at an oral dose equivalent to 1.3- and 13-times the MRHD (see Data).
Based on animal data, prostaglandins have been shown to have an important role in endometrial vascular permeability, blastocyst implantation, and decidualization. In animal studies, administration of prostaglandin synthesis inhibitors, such as meloxicam, resulted in increased pre- and post-implantation loss. Prostaglandins also have been shown to have an important role in fetal kidney development. In published animal studies, prostaglandin synthesis inhibitors have been reported to impair kidney development when administered at clinically relevant doses.
The estimated background risk of major birth defects and miscarriage for the indicated population(s) is unknown. All pregnancies have a background risk of birth defect, loss, or other adverse outcomes. In the U.S. general population, the estimated background risk of major birth defects and miscarriage in clinically recognized pregnancies is 2% to 4% and 15% to 20%, respectively.

Clinical Considerations

Fetal/Neonatal Adverse Reactions

Premature Closure of Fetal Ductus Arteriosus:

Avoid use of NSAIDs in women at about 30 weeks gestation and later in pregnancy, because NSAIDs, including XIFYRM, can cause premature closure of the fetal ductus arteriosus (see Data).

Oligohydramnios/Neonatal Renal Impairment:
If an NSAID is necessary at about 20 weeks gestation or later in pregnancy, limit the use to the lowest effective dose and shortest duration possible. If XIFYRM treatment extends beyond 48 hours, consider monitoring with ultrasound for oligohydramnios. If oligohydramnios occurs, discontinue XIFYRM and follow up according to clinical practice (see Data).

Labor or delivery
There are no studies on the effects of meloxicam during labor or delivery. In animal studies, NSAIDs, including meloxicam, inhibit prostaglandin synthesis, cause delayed parturition, and increase the incidence of stillbirth.

Data

Human Data

Premature Closure of Fetal Ductus Arteriosus:

Published literature reports that the use of NSAIDs at about 30 weeks of gestation and later in pregnancy may cause premature closure of the fetal ductus arteriosus.

Oligohydramnios/Neonatal Renal Impairment:
Published studies and postmarketing reports describe maternal NSAID use at about 20 weeks gestation or later in pregnancy associated with fetal renal dysfunction leading to oligohydramnios, and in some cases, neonatal renal impairment. These adverse outcomes are seen, on average, after days to weeks of treatment, although oligohydramnios has been infrequently reported as soon as 48 hours after NSAID initiation. In many cases, but not all, the decrease in amniotic fluid was transient and reversible with cessation of the drug. There have been a limited number of case reports of maternal NSAID use and neonatal renal dysfunction without oligohydramnios, some of which were irreversible. Some cases of neonatal renal dysfunction required treatment with invasive procedures, such as exchange transfusion or dialysis.
Methodological limitations of these postmarketing studies and reports include lack of a control group; limited information regarding dose, duration, and timing of drug exposure; and concomitant use of other medications. These limitations preclude establishing a reliable estimate of the risk of adverse fetal and neonatal outcomes with maternal NSAID use. Because the published safety data on neonatal outcomes involved mostly preterm infants, the generalizability of certain reported risks to the full-term infant exposed to NSAIDs through maternal use is uncertain.

Animal Data
Meloxicam was not teratogenic when administered to pregnant rats during fetal organogenesis at oral doses up to 4 mg/kg/day (1.3-times the MRHD of 30 mg based on body surface area (BSA) comparison). Administration of meloxicam to pregnant rabbits throughout embryogenesis produced an increased incidence of septal defects of the heart at an oral dose of 60 mg/kg/day (39-times the MRHD based on BSA comparison). The no effect level was 20 mg/kg/day (13-times the MRHD based on BSA comparison). In rats and rabbits, embryolethality occurred at oral meloxicam doses of 1 mg/kg/day and 5 mg/kg/day, respectively (0.32- and 3.24-times, respectively, the MRHD based on BSA comparison) when administered throughout organogenesis.
Oral administration of meloxicam to pregnant rats during late gestation through lactation increased the incidence of dystocia, delayed parturition, and decreased offspring survival at meloxicam doses of 0.125 mg/kg/day or greater (0.04-times the MRHD based on BSA comparison).

8.2 Lactation

Risk Summary
There are no human data available on whether meloxicam is present in human milk, or on the effects on breastfed infants, or on milk production. The developmental and health benefits of breastfeeding should be considered along with the mother’s clinical need for XIFYRM and any potential adverse effects on the breastfed infant from the XIFYRM or from the underlying maternal condition.

Data
Animal Data
Meloxicam was present in the milk of lactating rats at concentrations higher than those in plasma.

8.3 Females and Males of Reproductive Potential

Infertility
Females
Based on the mechanism of action, the use of prostaglandin-mediated NSAIDs, including XIFYRM, may delay or prevent rupture of ovarian follicles, which has been associated with reversible infertility in some women. Published animal studies have shown that administration of prostaglandin synthesis inhibitors has the potential to disrupt prostaglandin-mediated follicular rupture required for ovulation. Small studies in women treated with NSAIDs have also shown a reversible delay in ovulation. Consider withdrawal of NSAIDs, including XIFYRM, in women who have difficulties conceiving or who are undergoing investigation of infertility.

Males
XIFYRM may compromise fertility in males of reproductive potential. In a published study, oral administration of meloxicam to male rats for 35 days resulted in decreased sperm count and motility and histopathological evidence of testicular degeneration at 0.3-times the MRHD based on BSA comparison [see Nonclinical Toxicology (13.1)]. It is not known if these effects on fertility are reversible. The clinical relevance of these findings is unknown.

8.4 Pediatric Use

The safety and efficacy of XIFYRM has not been established in pediatric patients.

8.5 Geriatric Use

Elderly patients, compared to younger patients, are at greater risk for NSAID-associated serious cardiovascular, gastrointestinal, and/or renal adverse reactions. If the anticipated benefit for the elderly patient outweighs these potential risks monitor patients for adverse effects [see Warnings and Precautions (5.1, 5.2, 5.3, 5.6, 5.4)].
Of the total number of patients in clinical studies of meloxicam injection, 197 patients were age 65 and over. No overall differences in safety or effectiveness were observed between these patients and younger patients, and other reported clinical experience has not identified differences in responses between the elderly and younger patients.

8.6 Hepatic Impairment

XIFYRM has not been studied in patients with hepatic impairment. For oral meloxicam, no dose adjustment is necessary in patients with mild to moderate hepatic impairment. Since meloxicam is significantly metabolized in the liver and hepatotoxicity may occur, monitor for adverse events in patients with severe hepatic impairment [see Warnings and Precautions (5.3) and Clinical Pharmacology (12.3)].

8.7 Renal Impairment

Pharmacokinetics of meloxicam injection in elderly subjects with mild renal impairment is similar to healthy young subjects. Patients with moderate or severe renal impairment have not been studied. XIFYRM is not recommended in patients with moderate to severe renal insufficiency. XIFYRM is contraindicated in patients with moderate to severe renal insufficiency who are at risk for renal failure due to volume depletion [see Contraindications (4), Warnings and Precautions (5.6) and Clinical Pharmacology (12.3)].

8.8 Poor Metabolizers of CYP2C9 Substrates

In patients who are known or suspected to be poor CYP2C9 metabolizers based on genotype or previous history/experience with other CYP2C9 substrates (such as warfarin and phenytoin) consider dose reduction as they may have abnormally high plasma levels due to reduced metabolic clearance, and monitor patients for adverse effects.

10 OVERDOSAGE

Symptoms following acute NSAID overdoses have been typically limited to lethargy, drowsiness, nausea, vomiting, and epigastric pain, which have been generally reversible with supportive care. Gastrointestinal bleeding has occurred. Hypertension, acute renal failure, respiratory depression and coma have occurred, but were rare. [see Warnings and Precautions (5.1, 5.2, 5.4,5.6)].
Manage patients with symptomatic and supportive care following an NSAID overdosage. There are no specific antidotes. Forced diuresis, alkalinization of urine, hemodialysis, or hemoperfusion may be employed but are not likely to be useful due to high protein binding.
There is limited experience with meloxicam overdose. In four reported cases of meloxicam overdose, patients took 6 to 11 times the highest available oral dose of meloxicam tablets (15 mg); all recovered. Cholestyramine is known to accelerate the clearance of meloxicam.
Accelerated removal of meloxicam by 4 g doses of cholestyramine given three times a day was demonstrated in a clinical trial. Administration of cholestyramine may be useful following an overdosage.
In case of an overdosage, discontinue XIFYRM therapy and contact a regional poison control center at 1-800-222-1222.

11 DESCRIPTION

XIFYRM (meloxicam injection) is a nonsteroidal anti-inflammatory drug (NSAID). It is a sterile clear, pale-yellow to yellow color solution, containing the active pharmaceutical ingredient meloxicam for intravenous administration. Each mL of aqueous solution contains 30 mg of meloxicam, 150 mg of hydroxypropyl betadex, 20 mg of meglumine, 60 mg of povidone and water for injection. The pH of the meloxicam injection is 8.0 to 9.5.
The meloxicam drug substance is polymorph I. It is pale yellow powder. It is soluble in dimethylformamide, slightly soluble in acetone, very slightly soluble in ethanol 96% and in methanol, and practically insoluble in water.
Meloxicam is designated chemically as 4-hydroxy-2-methyl-N-(5-methyl-2-thiazolyl)-2H-1,2- benzothiazine-3-carboxamide-1,1-dioxide. The molecular weight is 351.4. Its molecular formula is C14H13N3O4S2 and the structural formula of meloxicam is:

12 CLINICAL PHARMACOLOGY

12.1 Mechanism of Action

Meloxicam has analgesic, anti-inflammatory, and antipyretic properties.
The mechanism of action of meloxicam, like that of other NSAIDs, is not completely understood but involves inhibition of cyclooxygenase (COX-1 and COX-2).
Meloxicam is a potent inhibitor of prostaglandin synthesis in vitro. Meloxicam concentrations reached during therapy have produced in vivo effects. Prostaglandins sensitize afferent nerves and potentiate the action of bradykinin in inducing pain in animal models. Prostaglandins are mediators of inflammation. Because meloxicam is an inhibitor of prostaglandin synthesis, its mode of action may be due to a decrease of prostaglandins in peripheral tissues.

12.2 Pharmacodynamics

Cardiac Electrophysiology
The effect of Meloxicam injection on QTc prolongation was evaluated in a randomized, double-blind, placebo-controlled crossover study in healthy subjects. A total of 48 subjects were administered intravenous meloxicam 30 mg, 120 mg, and 180 mg. In a study with demonstrated ability to detect small effects, the upper bound of the 90% confidence interval for the largest placebo- adjusted, baseline- corrected QTc based on Fridericia correction method (QTcF) was below 10 ms, the threshold for regulatory concern.

12.3 Pharmacokinetics

Absorption
Following single-dose intravenous administration of XIFYRM (meloxicam injection 30 mg/mL) to healthy adult volunteers, plasma concentrations of meloxicam was found comparable to that of another meloxicam injection 30 mg/mL. The single-dose pharmacokinetics (PK) of XIFYRM following intravenous administration is presented in Table 4.
Table 4. Single-dose PK of meloxicam injection from comparative bioavailability study

Pharmacokinetic parameters | XIFYRM (meloxicam injection) 30 mg/mL N=26 Mean ± SD | Meloxicam injection 30 mg/mL N=26 Mean ± SD
Cmax (μg/mL) | 8.755 ± 1.951 | 8.192 ± 1.739
AUCinf (μg.h/mL) | 118.923 ± 41.726 | 112.083 ± 36.689
Tmax (h)* | 0.045 (0.043 - 0.095) | 0.049 (0.043 - 4.000)
T1/2 (h) | 21.006 ± 5.608 | 20.358 ± 5.131

*Tmax values are reported as median (range).

Meloxicam injection exhibits linear pharmacokinetics over intravenous doses ranging from 15 mg to 180 mg.
Distribution
Following administration of meloxicam injection, the apparent volume of distribution during the terminal elimination phase (Vz) of meloxicam is 9.63 L.
Meloxicam is ~99.4% bound to human plasma proteins (primarily albumin) within the therapeutic dose range. The fraction of protein binding is independent of drug concentration, over the clinically relevant concentration range, but decreases to ~99% in patients with renal disease. Meloxicam penetration into human red blood cells, after oral dosing, is less than 10%. Following a radio labeled dose, over 90% of the radioactivity detected in the plasma was present as unchanged meloxicam.
Meloxicam concentrations in synovial fluid, after a single oral dose, range from 40% to 50% of those in plasma. The free fraction in synovial fluid is 2.5 times higher than in plasma, due to the lower albumin content in synovial fluid as compared to plasma. The significance of this penetration is unknown.
Elimination
Metabolism
Meloxicam is extensively metabolized in the liver. Meloxicam metabolites include 5'-carboxy meloxicam (60% of dose), from P-450 mediated metabolism formed by oxidation of an intermediate metabolite 5'-hydroxymethyl meloxicam which is also excreted to a lesser extent (9% of dose). In vitro studies indicate that CYP2C9 (cytochrome P450 metabolizing enzyme) plays an important role in this metabolic pathway with a minor contribution of the CYP3A4 isozyme. Patients’ peroxidase activity is probably responsible for the other two metabolites which account for 16% and 4% of the administered dose, respectively. The four metabolites are not known to have any in vivo pharmacological activity.
Excretion
Meloxicam excretion is predominantly in the form of metabolites, and occurs to equal extents in the urine and feces. Only traces of the unchanged parent compound are excreted in the urine (0.2%) and feces (1.6%). The extent of the urinary excretion was confirmed for unlabeled multiple 7.5 mg doses: 0.5%, 6%, and 13% of the dose were found in urine in the form of meloxicam, and the 5'-hydroxymethyl and 5'-carboxy metabolites, respectively. There is significant biliary and/or enteral secretion of the drug. This was demonstrated when oral administration of cholestyramine following a single IV dose of meloxicam decreased the AUC of meloxicam by 50%.
The mean elimination half-life (t1/2) for XIFYRM 30 mg is approximately 21 hours.
Specific Populations
Based on population pharmacokinetics analyses, age, sex and race do not have a clinically meaningful effect on the PK of meloxicam injection.
Hepatic Impairment: The pharmacokinetics of XIFYRM have not been investigated in patients with hepatic impairment. However, following a single 15 mg dose of meloxicam tablets there was no marked difference in plasma concentrations in patients with mild (Child-Pugh Class I) or moderate (Child-Pugh Class II) hepatic impairment compared to healthy volunteers. Protein binding of meloxicam was not affected by hepatic impairment. No dosage adjustment is necessary in patients with mild to moderate hepatic impairment. Patients with severe hepatic impairment (Child-Pugh Class III) have not been adequately studied. Monitor for adverse events when used in patients with severe hepatic impairment. [see Warnings and Precautions (5.3), Use in Specific Populations (8.6)].
Renal Impairment: Meloxicam pharmacokinetics have been investigated in elderly subjects with mild renal impairment (eGFR 60 – 90) compared to young healthy volunteers. A 5% and 7% increase of Cmax and AUC, respectively, was observed in elderly subjects with mild renal impairment. No dosage adjustment is necessary in patients with mild renal impairment. Patients with moderate and severe renal impairment have not been adequately studied. The use of XIFYRM in patients with moderate to severe renal impairment is not recommended. XIFYRM is contraindicated in patients with moderate to severe renal insufficiency who are at risk for renal failure due to volume depletion [see Contraindications (4), Warnings and Precautions (5.6), Use in Specific Populations (8.7)].
Drug Interaction Studies
Aspirin: When NSAIDs were administered with aspirin, the protein binding of NSAIDs were reduced, although the clearance of free NSAID was not altered. The clinical significance of this interaction is not known. See Table 3 clinically significant drug interactions of NSAIDs with aspirin [see Drug Interactions (7)].
Cholestyramine: Pretreatment for four days with cholestyramine significantly increased the clearance of meloxicam by 50%. This resulted in a decrease in t1/2, from 19.2 hours to 12.5 hours, and a 35% reduction in AUC. This suggests the existence of a recirculation pathway for meloxicam in the gastrointestinal tract. The clinical relevance of this interaction has not been established.
Cimetidine: Concomitant administration of 200 mg cimetidine four times daily did not alter the single-dose pharmacokinetics of 30 mg meloxicam.
Digoxin: Meloxicam tablets 15 mg once daily for 7 days did not alter the plasma concentration profile of digoxin after β-acetyldigoxin administration for 7 days at clinical doses. In vitro testing found no protein binding drug interaction between digoxin and meloxicam [see Drug Interactions (7)].
Lithium: In a study conducted in healthy subjects, mean pre-dose lithium concentration and AUC were increased by 21% in subjects receiving lithium doses ranging from 804 to 1072 mg twice daily with meloxicam tablets 15 mg once per day every day as compared to subjects receiving lithium alone [see Drug Interactions (7)].
Methotrexate: A study in 13 rheumatoid arthritis (RA) patients evaluated the effects of multiple oral doses of meloxicam on the pharmacokinetics of methotrexate taken once weekly.
Meloxicam did not have a significant effect on the pharmacokinetics of single doses of methotrexate. In vitro, methotrexate did not displace meloxicam from its human serum binding sites [see Drug Interactions (7)].
Warfarin: The effect of meloxicam tablets on the anticoagulant effect of warfarin was studied in a group of healthy subjects receiving daily doses of warfarin that produced an INR (International Normalized Ratio) between 1.2 and 1.8. In these subjects, meloxicam did not alter warfarin pharmacokinetics and the average anticoagulant effect of warfarin as determined by prothrombin time. However, one subject showed an increase in INR from 1.5 to 2.1. Caution should be used when administering XIFYRM with warfarin since patients on warfarin may experience changes in INR and an increased risk of bleeding complications when a new medication is introduced [see Drug Interactions (7)].

12.5 Pharmacogenomics

CYP2C9 activity is reduced in individuals with genetic variants such as CYP2C9*2 and CYP2C9*3 polymorphisms. Limited data from three published reports showed that meloxicam AUC was substantially higher in individuals with reduced CYP2C9 activity, particularly in poor metabolizers (e.g., *3/*3), compared to normal metabolizers (*1/*1). The frequency of CYP2C9 poor metabolizer genotypes varies based on racial/ethnic background but is generally present in <5% of the population.

13 NONCLINICAL TOXICOLOGY

13.1 Carcinogenesis, Mutagenesis, Impairment Of Fertility

Carcinogenesis
There was no increase in tumor incidence in long-term carcinogenicity studies in rats (104 weeks) and mice (99 weeks) administered meloxicam at oral doses up to 0.8 mg/kg/day in rats and up to 8.0 mg/kg/day in mice (up to 0.26- and 1.3-times, respectively, the MRHD of 30 mg/day of XIFYRM based on BSA comparison).
Mutagenesis
Meloxicam was not mutagenic in an Ames assay. Meloxicam was not clastogenic in a chromosome aberration assay with human lymphocytes and an in vivo micronucleus test in mouse bone marrow.
Impairment of Fertility
Meloxicam did not impair male and female fertility in rats at oral doses up to 9 mg/kg/day in males and 5 mg/kg/day in females (up to 2.9- and 1.6-times, respectively, the MRHD based on BSA comparison).
In a published study, oral administration of 1 mg/kg (0.3-times the MRHD based on BSA comparison) meloxicam to male rats for 35 days resulted in decreased sperm count and motility and histopathological evidence of testicular degeneration. The clinical relevance of these findings is unknown.

14 CLINICAL STUDIES

The efficacy and safety of meloxicam injection in the treatment of moderate to severe pain was evaluated in two Phase 3 randomized, double-blind, placebo-controlled, multiple-dose clinical trials in patients with postoperative pain. In both trials, oral oxycodone 5 mg was permitted as rescue medication for pain management.
Study 1 (Bunionectomy Surgery)
In the first controlled, multiple-dose trial (NCT02675907) of adult patients with postoperative pain who underwent bunionectomy surgery, 201 patients were treated with meloxicam injection 30 mg or placebo administered once daily for two days starting on the day after surgery. An optional third dose was permitted just prior to discharge. A minimum postoperative baseline pain intensity of 4 on the Numeric Pain Rating Scale (NPRS) (range 0-10) and pain categorized as moderate or severe were required for randomization. The majority of patients were female (85%). The average age was 48 years. The mean overall baseline pain intensity on the NPRS was 6.8. A statistically significant difference demonstrating efficacy was observed in the primary efficacy endpoint of the summed pain intensity difference over the first 48 hours (SPID48). The average pain intensity over time is depicted for the treatment groups in Figure 2. A generally consistent separation in pain scores between the meloxicam injection and placebo groups was observed from time of onset through most of the dosing interval with a narrowing at the end of the first 24-hour dosing interval.

Study 2 (Abdominoplasty Surgery)
In the second controlled, multiple-dose trial (NCT02678286) of adult patients with postoperative pain who underwent elective abdominoplasty surgery, 219 patients were treated with meloxicam injection 30 mg or placebo administered once daily for two days starting on the day of surgery. An optional third dose was permitted just prior to discharge. A minimum postoperative baseline pain intensity of 4 on the NPRS (range 0-10) and pain categorized as moderate or severe were required for randomization. The majority of patients were female (98%). The average age was 40 years. The mean overall baseline pain intensity on the NPRS was 7.3. A statistically significant difference demonstrating efficacy was observed in the primary efficacy endpoint of the summed pain intensity difference over the first 24 hours (SPID24) as well as over the first 48 hours (SPID48). The average pain intensity over time is depicted for the treatment groups in Figure 3. A generally consistent separation in pain scores between the meloxicam injection and placebo group was observed from time of onset through most of the dosing interval with a narrowing at the end of the first 24-hour dosing interval.

Onset of Meaningful Pain Relief and Use of Rescue Analgesic Medication

The median time to first rescue analgesic use in patients treated with meloxicam injection (2 hours in Study 1 and 1 hour in Study 2) came before the median time to patient-reported meaningful pain relief in both studies (2 hours in Study 1 and 3 hours in Study 2). Fifty percent of patients treated with meloxicam injection and 49% of patients treated with placebo in Study 1 received rescue analgesia medication in the first 2 hours after the start of dosing. Seventy-eight percent of patients treated with meloxicam injection and 78% of patients treated with placebo in Study 2 received rescue in the first 3 hours after the start of dosing.

16 HOW SUPPLIED/STORAGE AND HANDLING

XIFYRM (meloxicam injection) is a clear, pale-yellow to yellow color solution intended for intravenous use supplied as a 1 mL fill (30 mg/mL) in a clear, single-dose vial with a blue tamper-evident top.

NDC Number | Package Size
24338-153-02 | 10 x 1 mL Single-Dose Vials
24338-153-01 | 1 mL Single-Dose Vial

Store at 20°C to 25°C (68°F to 77°F); excursions permitted to 15°C to 30°C (59°F to 86°F) [see USP Controlled Room Temperature]. Keep vial in carton to protect from light.

Discard unused portion.

17 PATIENT COUNSELING INFORMATION

Inform patients of the following information before initiating therapy with XIFYRM.
Cardiovascular Thrombotic Effects
Advise patients to be alert for the symptoms of cardiovascular thrombotic events, including chest pain, shortness of breath, weakness, or slurring of speech, and to report any of these symptoms to their healthcare provider immediately [see Warnings and Precautions (5.1)].
Gastrointestinal Bleeding, Ulceration, and Perforation
Advise patients to report symptoms of ulcerations and bleeding, including epigastric pain, dyspepsia, melena, and hematemesis to their healthcare provider. In the setting of concomitant use of low-dose aspirin for cardiac prophylaxis, inform patients of the increased risk for the signs and symptoms of GI bleeding [see Warnings and Precautions (5.2)].
Hepatotoxicity
Inform patients of the warning signs and symptoms of hepatotoxicity (e.g., nausea, fatigue, lethargy, diarrhea, pruritus, jaundice, right upper quadrant tenderness, and "flu-like" symptoms). If these occur, instruct patients to stop XIFYRM and seek immediate medical therapy [see Warnings and Precautions (5.3)].
Heart Failure and Edema
Advise patients to be alert for the symptoms of congestive heart failure including shortness of breath, unexplained weight gain, or edema and to contact their healthcare provider if such symptoms occur [see Warnings and Precautions (5.5)].
Anaphylactic Reactions
Inform patients of the signs of an anaphylactic reaction (e.g., difficulty breathing, swelling of the face or throat). Instruct patients to seek immediate emergency help if these occur [see Contraindications (4) and Warnings and Precautions (5.7)].
Serious Skin Reactions including DRESS
Advise patients to stop taking XIFYRM immediately if they develop any type of rash or fever and to contact their healthcare provider as soon as possible [see Warnings and Precautions (5.9,5.10)].
Female Fertility
Advise females of reproductive potential who desire pregnancy that NSAIDs, including XIFYRM, may be associated with a reversible delay in ovulation [see Use in Specific Populations (8.3)].
Fetal Toxicity
Inform pregnant women to avoid use of XIFYRM and other NSAIDs starting at 30 weeks gestation because of the risk of the premature closing of the fetal ductus arteriosus. If treatment with XIFYRM is needed for a pregnant woman between about 20 to 30 weeks gestation, advise her that she may need to be monitored for oligohydramnios, if treatment continues for longer than 48 hours [see Warnings and Precautions (5.11) and Use in Specific Populations (8.1)].
Avoid Concomitant Use of NSAIDs
Inform patients that the concomitant use of XIFYRM with other NSAIDs or salicylates (e.g., diflunisal, salsalate) is not recommended due to the increased risk of gastrointestinal toxicity, and little or no increase in efficacy [see Warnings and Precautions (5.2) and Drug Interactions (7)]. Alert patients that NSAIDs may be present in “over the counter” medications for treatment of colds, fever, or insomnia.
Use of NSAIDs and Low-Dose Aspirin
Inform patients not to use low-dose aspirin concomitantly with XIFYRM until they talk to their healthcare provider [see Drug Interactions (7)].
This Prescribing Information has been approved by the US Food and Drug Administration.
Distributed by:
Azurity Pharmaceuticals, Inc.
Woburn, MA 01801

06/2025 Rev00

PACKAGE LABEL.PRINCIPAL DISPLAY PANEL

XIFYRM (meloxicam injection) 30 mg/mL - Carton Label

NDC 24338-153-02

10 x 1 mL Single-Dose Vials

PRINCIPAL DISPLAY PANEL - VIAL LABEL

XIFYRM (meloxicam injection) 30 mg/mL

NDC: 24338-153-01

1mL Single-Dose Vial